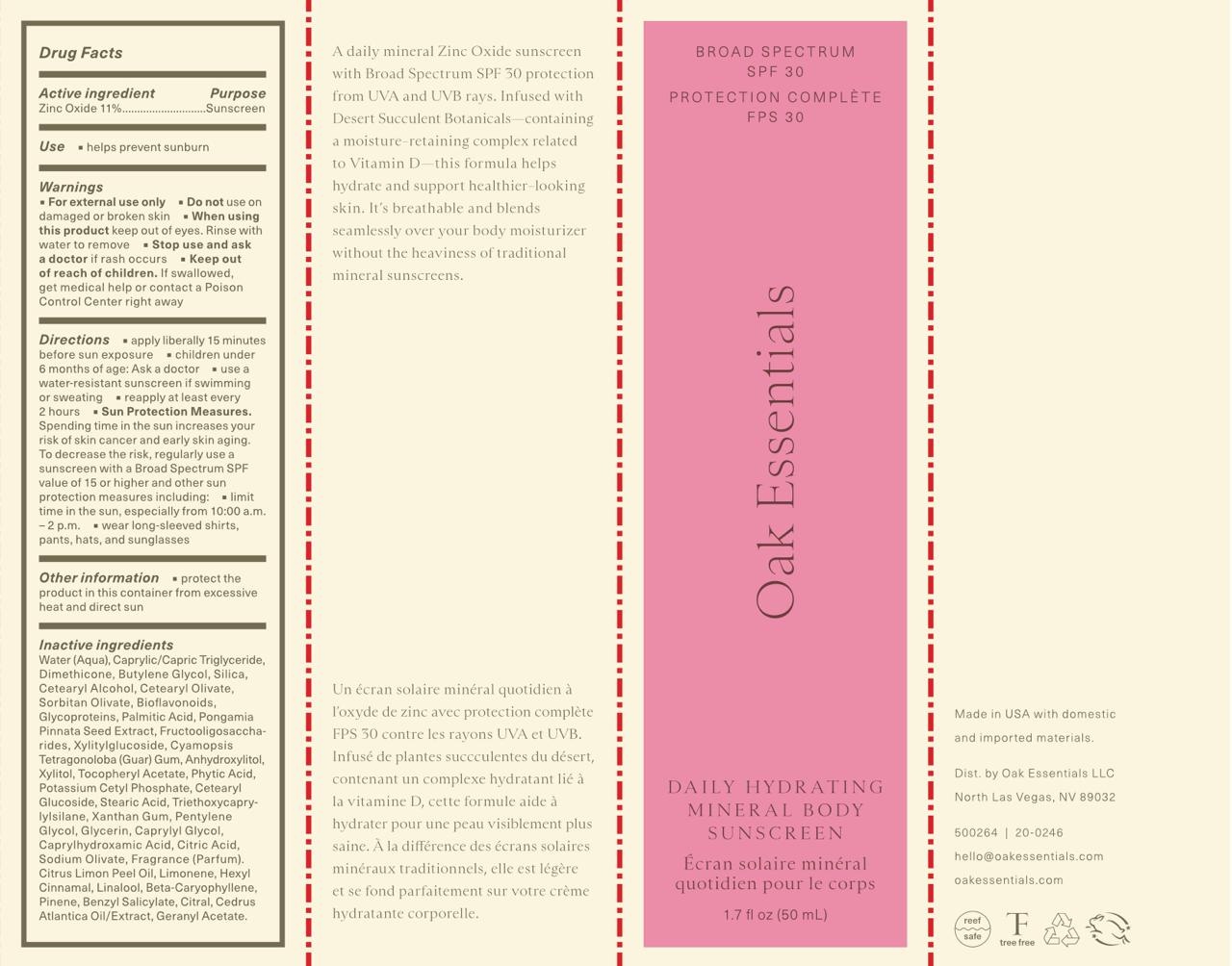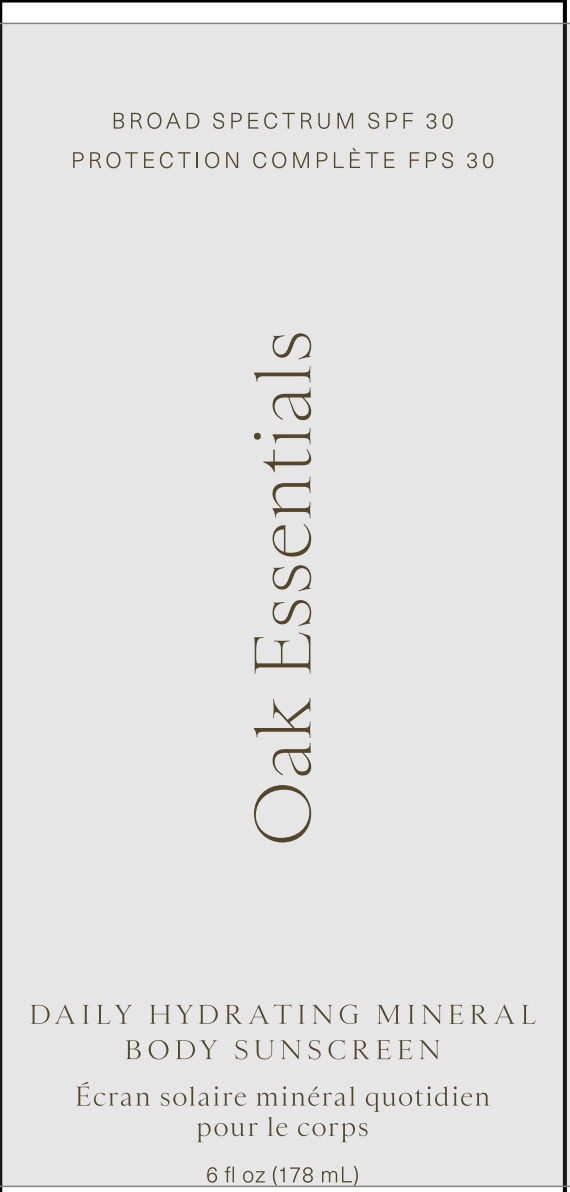 DRUG LABEL: Daily Hydrating Mineral Body Sunscreen
NDC: 87330-101 | Form: CREAM
Manufacturer: Oak Essentials, LLC
Category: otc | Type: HUMAN OTC DRUG LABEL
Date: 20260107

ACTIVE INGREDIENTS: ZINC OXIDE 11 g/100 mL
INACTIVE INGREDIENTS: CETEARYL GLUCOSIDE; STEARIC ACID; PONGAMIA PINNATA WHOLE; LITHOPS PSEUDOTRUNCATELLA CULTURED GLYCOCALYX LYSATE; CETEARYL OLIVATE; SILICON DIOXIDE; BENZYL SALICYLATE; CAPRYLYL GLYCOL; PALMITIC ACID; TRIETHOXYCAPRYLYLSILANE; GLYCERIN; CITRUS BIOFLAVONOIDS; LEMON OIL, COLD PRESSED; CETEARYL ALCOHOL; XYLITYLGLUCOSIDE; DIMETHICONE; CAPRYLIC/CAPRIC TRIGLYCERIDE; .ALPHA.-HEXYLCINNAMALDEHYDE; LINALOOL, (+/-)-; POTASSIUM CETYL PHOSPHATE; SORBITAN OLIVATE; PENTYLENE GLYCOL; CAPRYLHYDROXAMIC ACID; CARYOPHYLLENE; .ALPHA.-TOCOPHEROL ACETATE; SODIUM OLIVATE; CITRIC ACID; BUTYLENE GLYCOL; WATER; LONGIFOLENE; LIME OIL, DISTILLED; XYLITOL; XANTHAN GUM; CYAMOPSIS TETRAGONOLOBA (GUAR) GUM; ANHYDROXYLITOL; PHYTIC ACID

Oak Essentials (as PLD): Daily Hydrating Mineral Body Sunscreen (87330-101)

Active Ingredient

Zinc Oxide 11%

Purpose

Sunscreen

Use

- Helps prevent sunburn

Warnings

- For external use only.

- Do not use on damaged or broken skin

- When using this product keep out of eyes. Rinse with water to remove.

- Stop use and ask a doctor if rash occurs

- Keep out of reach of children. If product is swallowed, get medical help or contact a Poison Control Center right away.

Directions

- apply liberally 15 minutes before sun exposure
- children under 6 months of age: Ask a doctor
- use a water-resistant sunscreen if swimming or sweating
- reapply at least every 2 hours
- Sun Protection Measures. Spending time in the sun increases your risk of skin cancer and early skin aging. To decrease this risk, regularly use a sunscreen with a Broad Spectrum SPF value of 15 or higher and other sun protection measures including:
- limit time in the sun, especially from 10 a.m. - 2 p.m.
- wear long-sleeved shirts, pants, hats, and sunglasses

Other information

- protect the product in this container from excessive heat and direct sun

Inactive ingredients

Water (Aqua), Caprylic/Capric Triglyceride, Dimethicone, Butylene Glycol, Silica, Cetearyl Alcohol, Cetearyl Olivate, Sorbitan Olivate, Potassium Cetyl Phosphate, Xylitylglucoside, Caprylyl Glycol, Anhydroxylitol, Cetearyl Glucoside, Palmitic Acid, Triethoxycaprylylsilane, Stearic Acid, Xylitol, Glycerin, Pongamia Pinnata Seed Extract, Caprylhydroxamic Acid, Xanthan Gum, Tocopheryl Acetate, Citric Acid, Bioflavonoids, Glycoproteins, Fructooligosaccharides, Pentylene Glycol, Sodium Olivate, Cyamopsis Tetragonoloba (Guar) Gum, Phytic Acid, Fragrance (Parfum).